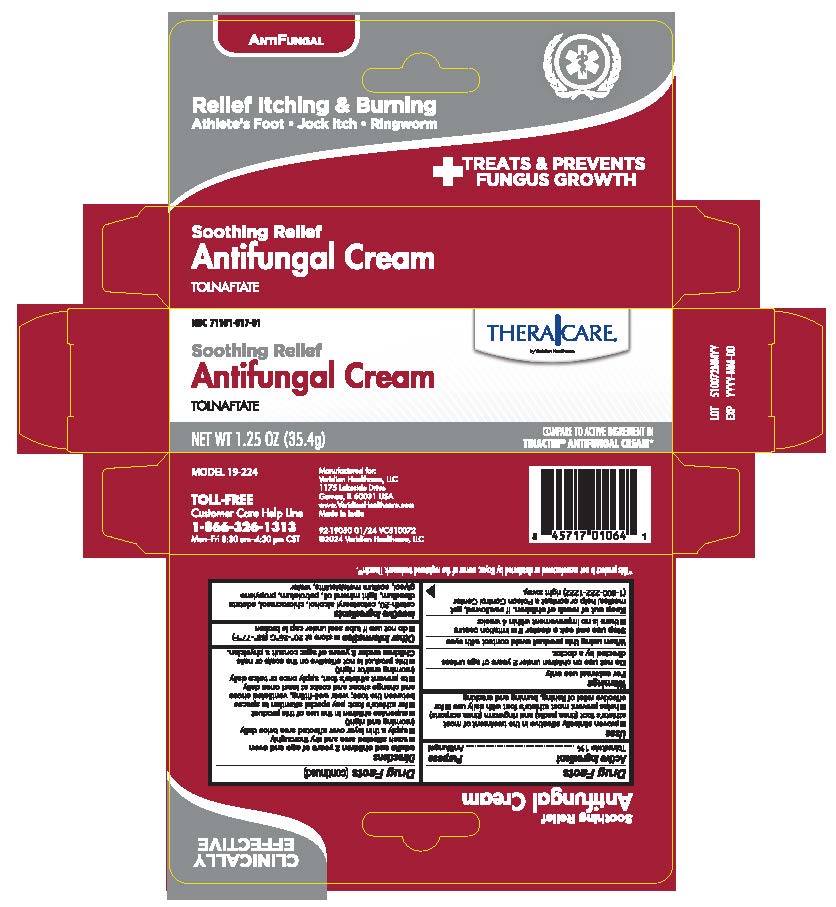 DRUG LABEL: TheraCare Antifungal Cream
NDC: 71101-017 | Form: CREAM
Manufacturer: Veridian Healthcare
Category: otc | Type: HUMAN OTC DRUG LABEL
Date: 20260129

ACTIVE INGREDIENTS: TOLNAFTATE 10 mg/1 g
INACTIVE INGREDIENTS: CETETH-20; CETOSTEARYL ALCOHOL; CHLOROCRESOL; LIGHT MINERAL OIL; PROPYLENE GLYCOL; WATER; EDETATE DISODIUM; PETROLATUM; SODIUM METABISULFITE

TheraCare Antifungal Cream

Drug Facts

Active ingredient

Tolnaftate 1%

Purpose

Antifungal

Uses

- proven clinically effective in the treatment of most athlete's foot (tinea pedis) and ringworm (tinea corporis)
- helps prevent most athlete's foot with daily use
- for effective relief of itching, burning and cracking

Warnings

For external use only

Do not use on children under 2 years of age unless directed by a doctor

When using this productavoid contact with the eyes

Stop use and ask a doctor if

- irritation occurs
- there is no improvement within 4 weeks

Keep out of reach of children.If swallowed, get medical help or contact a Poison Control Center right away. (1-800-222-1222)

Directions

adults and children 2 years of age and over:

- wash affected area and dry thoroughly
- apply a thin layer over affected area twice daily (morning and night)
- supervise children in the use of this product
- for athlete's foot: pay special attention to spaces between the toes; wear well-fitting, ventilated shoes and change shoes and socks at least once daily
- to prevent athlete's foot, apply once or twice daily (morning and/or night)
- this product is not effective on the scalp or nails

Children under 2 years of age: consult a physician

Other information

store between 20° to 25°C (68° to 77°F)

- do not use if tube seal under cap is broken

Inactive ingredients

ceteth-20, cetostearyl alcohol, chlorocresol, edetate disodium, light mineral oil, petrolatum, propylene glycol, sodium matabisulfite, water

Questions?

Toll Free 1-866-326-1313